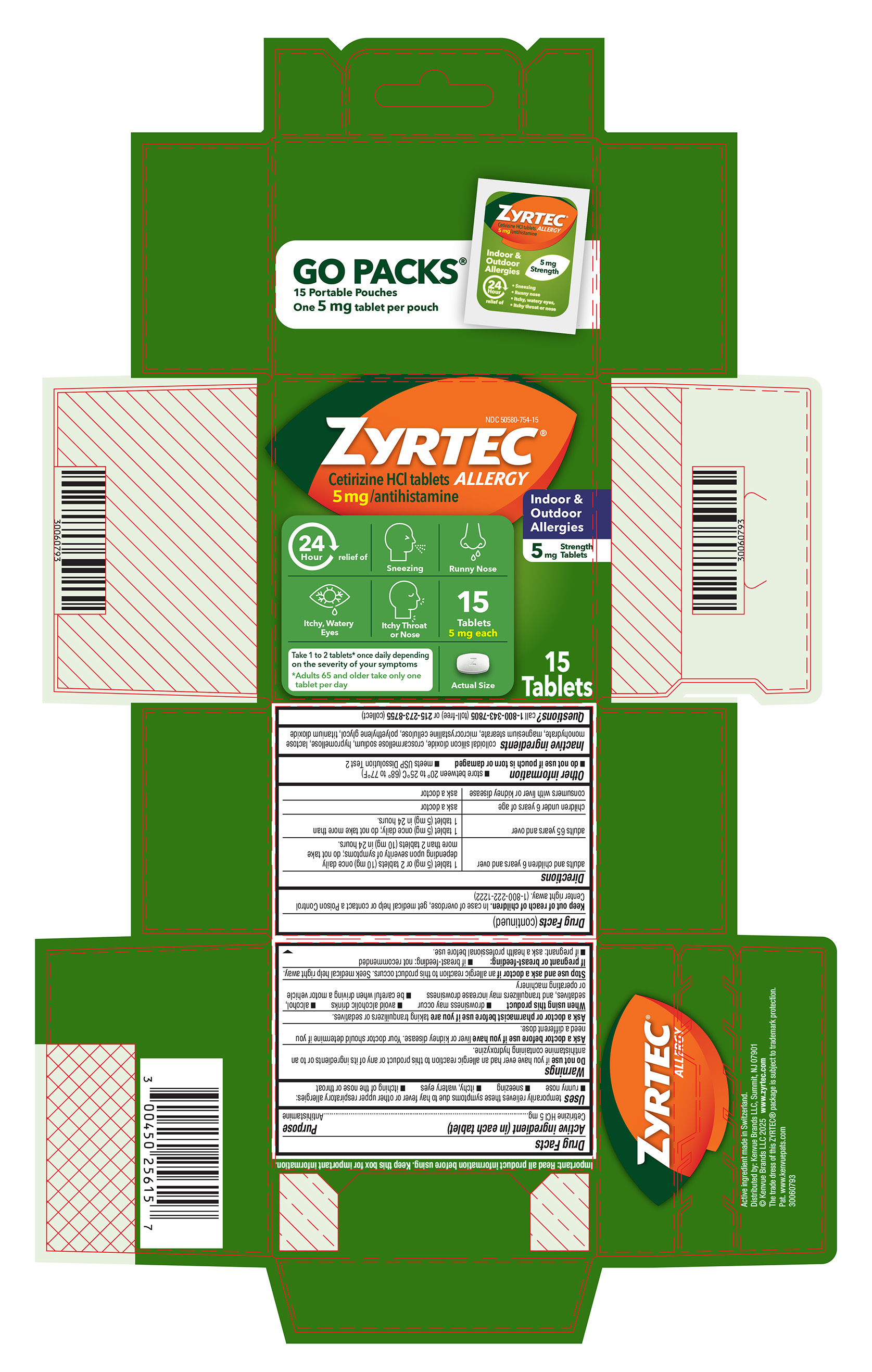 DRUG LABEL: Zyrtec Allergy
NDC: 50580-754 | Form: TABLET, FILM COATED
Manufacturer: Kenvue Brands LLC
Category: otc | Type: HUMAN OTC DRUG LABEL
Date: 20250721

ACTIVE INGREDIENTS: CETIRIZINE HYDROCHLORIDE 5 mg/1 1
INACTIVE INGREDIENTS: POLYETHYLENE GLYCOL, UNSPECIFIED; TITANIUM DIOXIDE; LACTOSE MONOHYDRATE; SILICON DIOXIDE; CROSCARMELLOSE SODIUM; HYPROMELLOSE, UNSPECIFIED; MAGNESIUM STEARATE; MICROCRYSTALLINE CELLULOSE

Zyrtec Allergy

Drug Facts

Active ingredient (in each tablet)

Cetirizine HCl 5 mg

Purpose

Antihistamine

Uses

temporarily relieves these symptoms due to hay fever or other upper respiratory allergies:

- runny nose
- sneezing
- itchy, watery eyes
- itching of the nose or throat

Warnings

Do not use if you have ever had an allergic reaction to this product or any of its ingredients or to an antihistamine containing hydroxyzine.

Ask a doctor before use if you have liver or kidney disease. Your doctor should determine if you need a different dose.

Ask a doctor or pharmacist before use if you are taking tranquilizers or sedatives.

When using this product
■ drowsiness may occur ■ avoid alcoholic drinks
■ alcohol, sedatives, and tranquilizers may increase drowsiness
■ be careful when driving a motor vehicle or operating machinery

Stop use and ask a doctor if an allergic reaction to this product occurs. Seek medical help right away.

If pregnant or breast-feeding:
■ if breast-feeding: not recommended ■ if pregnant: ask a health professional before use.

Keep out of reach of children. In case of overdose, get medical help or contact a Poison Control Center right away. (1-800-222-1222)

Directions

adults and children 6 years and over | 1 tablet (5 mg) or 2 tablets (10 mg) once daily depending upon severity of symptoms; do not take more than 2 tablets (10mg) in 24 hours.
adults 65 years and over | 1 tablet (5 mg) once daily; do not take more than 1 tablet (5 mg) in 24 hours.
children under 6 years of age | ask a doctor
consumers with liver or kidney disease | ask a doctor

Other information

■ store between 20° to 25°C (68° to 77°F)
■ do not use if pouch is torn or damaged
■ meets USP Dissolution Test 2

Inactive ingredients

colloidal silicon dioxide, croscarmellose sodium, hypromellose, lactose monohydrate, magnesium stearate, microcrystalline cellulose, polyethylene glycol, titanium dioxide

Questions?

call 1-800-343-7805 (toll-free) or 215-273-8755 (collect)

PRINCIPAL DISPLAY PANEL

NDC 50580-754-15

ZYRTEC®

ALLERGY

Cetirizine HCl Tablets
5mg/antihistamine

Indoor &
Outdoor
Allergies
5mg Strength Tablets

24 Hour relief of

- Sneezing
- Runny Nose
- Itchy, Watery Eyes
- Itchy Throat or Nose

15 Tablets
5 mg each

Take 1 to 2 tablets* once daily depending on the severity of your symptoms
*Adults 65 and older take only one tablet per day

Actual Size

15 Tablets